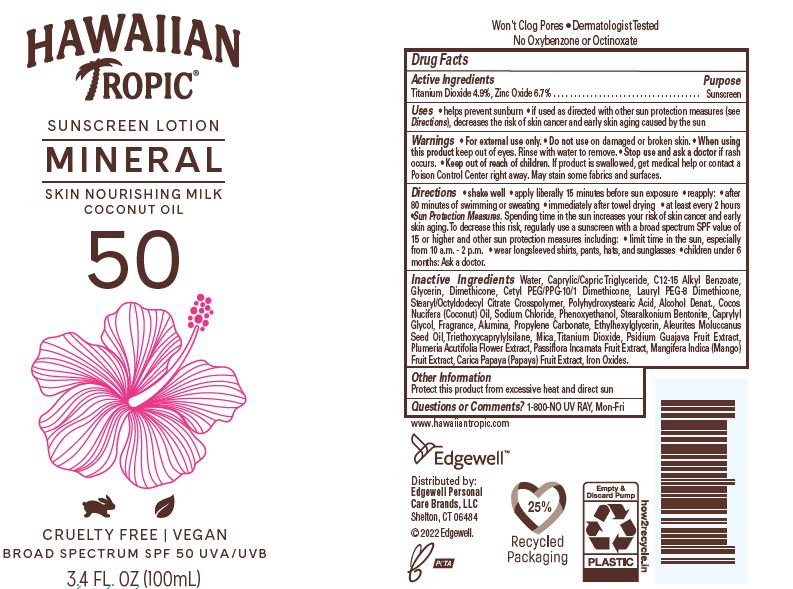 DRUG LABEL: Hawaiian Tropic Mineral Skin Nourishing Milk Coconut Oil SPF 50
NDC: 63354-703 | Form: OIL
Manufacturer: Edgewell Personal Care Brands LLC
Category: otc | Type: HUMAN OTC DRUG LABEL
Date: 20251106

ACTIVE INGREDIENTS: ZINC OXIDE 6.7 g/100 g; TITANIUM DIOXIDE 4.9 g/100 g
INACTIVE INGREDIENTS: ALKYL (C12-15) BENZOATE; DIMETHICONE; CETYL PEG/PPG-10/1 DIMETHICONE (HLB 2); ALUMINUM OXIDE; PROPYLENE CARBONATE; MICA; GUAVA; PLUMERIA RUBRA FLOWER; PAPAYA; KUKUI NUT OIL; ETHYLHEXYLGLYCERIN; PASSIFLORA INCARNATA FRUIT; CAPRYLYL GLYCOL; WATER; COCONUT OIL; FERRIC OXIDE YELLOW; GLYCERIN; MEDIUM-CHAIN TRIGLYCERIDES; MANGO; TRIETHOXYCAPRYLYLSILANE; DEHYDRATED ALCOHOL; SODIUM CHLORIDE; PHENOXYETHANOL; POLYHYDROXYSTEARIC ACID (2300 MW); STEARYL/OCTYLDODECYL CITRATE CROSSPOLYMER

Active Ingredients

Titanium Dioxide 4.9%, Zinc Oxide 6.7% .

Purpose

Sunscreen

Uses

• helps prevent sunburn • if used as directed with other sun protection measures (see Directions), decreases the risk of skin cancer and early skin aging caused by the sun

Warnings

For external use only.

May stain some fabrics and surfaces.

Do not use

on damaged or broken skin.

When using this product

keep out of eyes. Rinse with water to remove.

Stop use and ask a doctor

if rash occurs.

Keep out of reach of children

If product is swallowed, get medical help or contact a Poison Control Center right away

Directions

• shake well • apply liberally 15 minutes before sun exposure • reapply: • after
80 minutes of swimming or sweating • immediately after towel drying • at least every 2 hours
•Sun Protection Measures. Spending time in the sun increases your risk of skin cancer and early
skin aging. To decrease this risk, regularly use a sunscreen with a broad spectrum SPF value of
15 or higher and other sun protection measures including: • limit time in the sun, especially
from 10 a.m. - 2 p.m. • wear longsleeved shirts, pants, hats, and sunglasses • children under 6
months: Ask a doctor.

Inactive Ingredients

Water, Caprylic/Capric Triglyceride, C12-15 Alkyl Benzoate, Glycerin, Dimethicone, Cetyl PEG/PPG-10/1 Dimethicone, Lauryl PEG-8 Dimethicone, Stearyl/Octyldodecyl Citrate Crosspolymer, Polyhydroxystearic Acid, Alcohol Denat., Cocos Nucifera (Coconut) Oil, Sodium Chloride, Phenoxyethanol, Stearalkonium Bentonite, Caprylyl Glycol, Fragrance, Alumina, Propylene Carbonate, Ethylhexylglycerin, Aleurites Moluccanus Seed Oil, Triethoxycaprylylsilane, Mica, Titanium Dioxide, Psidium Guajava Fruit Extract,
Plumeria Acutifolia Flower Extract, Passiflora Incarnata Fruit Extract, Mangifera Indica (Mango) Fruit Extract, Carica Papaya (Papaya) Fruit Extract, Iron Oxides.

Other Information

Protect this product from excessive heat and direct sun

Questions or Comments?

1-800-NO UV RAY, Mon-Fri

PRINCIPAL DISPLAY PANEL

HAWAIIAN

TROPIC

SUNSCREEN LOTION

MINERAL

SKIN NOURISHING MILK

50

CRUELTY FREE | VEGAN
BROAD SPECTRUM SPF 50 UVA/UVB

3.4 FL. OZ (100mL)